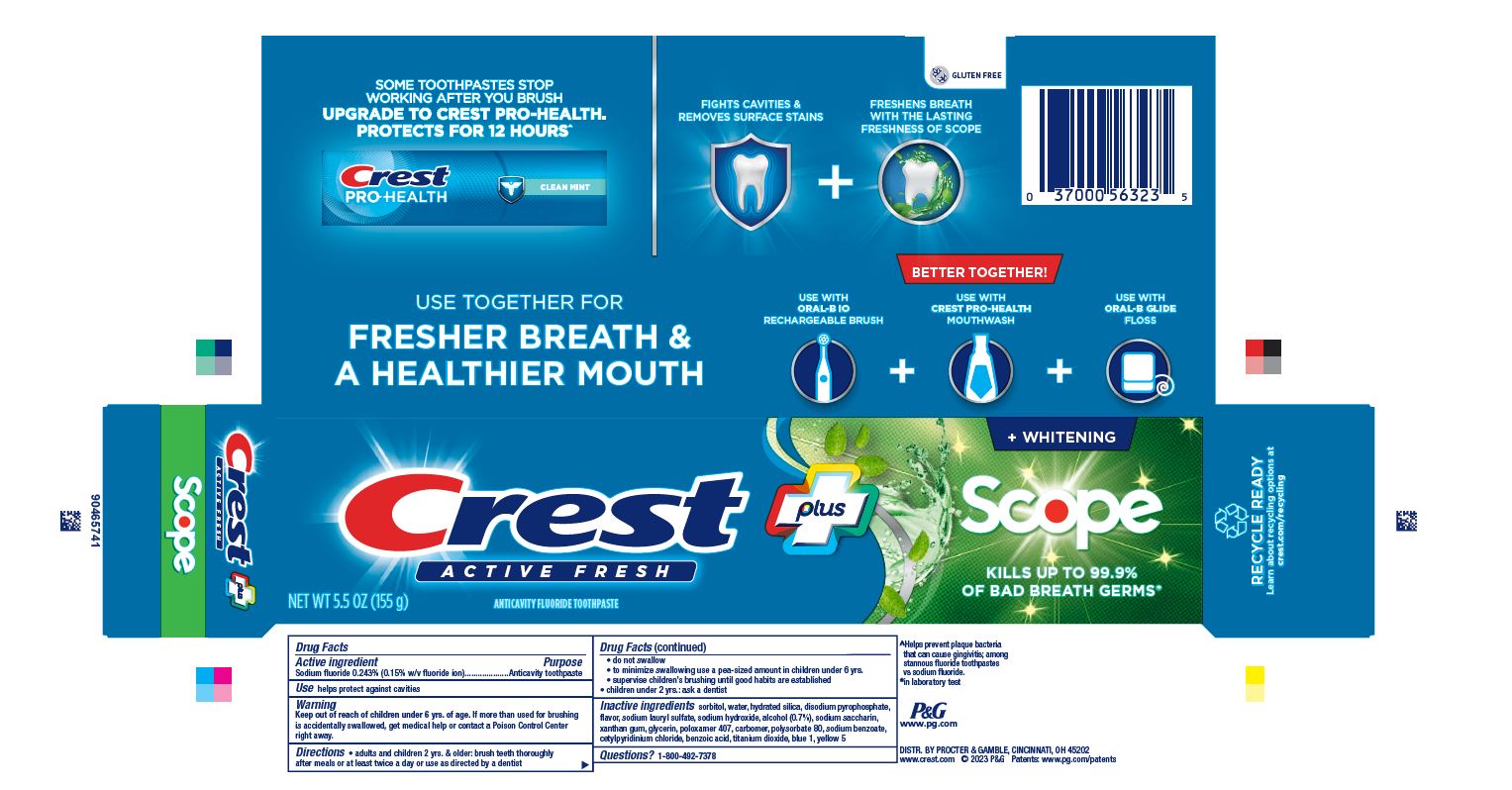 DRUG LABEL: Crest Plus
NDC: 69423-823 | Form: PASTE, DENTIFRICE
Manufacturer: The Procter & Gamble Manufacturing Company
Category: otc | Type: HUMAN OTC DRUG LABEL
Date: 20260106

ACTIVE INGREDIENTS: SODIUM FLUORIDE 1.5 mg/1 g
INACTIVE INGREDIENTS: SODIUM HYDROXIDE; XANTHAN GUM; SACCHARIN SODIUM; POLOXAMER 407; CARBOXYPOLYMETHYLENE; SORBITOL; WATER; HYDRATED SILICA; SODIUM LAURYL SULFATE; ALCOHOL; FD&C YELLOW NO. 5; GLYCERIN; POLYSORBATE 80; SODIUM BENZOATE; CETYLPYRIDINIUM CHLORIDE; BENZOIC ACID; TITANIUM DIOXIDE; FD&C BLUE NO. 1; SODIUM ACID PYROPHOSPHATE

Crest Plus Active Fresh + Whitening Scope

Drug Facts

Active ingredient

Sodium fluoride 0.243%

(0.15% w/v fluoride ion)

Purpose

Anticavity toothpaste

Use

helps protect against cavities

Warnings

Keep out of reach of children under 6 yrs. of age.If more than used for brushing is accidentally swallowed, get medical help or contact a Poison Control Center right away.

Directions

- adults and children 2 yrs. & older: brush teeth thoroughly after meals or at least twice a day or use as directed by a dentist
- do not swallow
- to minimize swallowing use a pea-sized amount in children under 6
- supervise children's brushing until good habits are established
- children under 2 yrs.: ask a dentist

Inactive ingredients

sorbitol, water, hydrated silica, disodium pyrophosphate, flavor, sodium lauryl sulfate, sodium hydroxide, alcohol (0.7%), sodium saccharin, xanthan gum, glycerin, poloxamer 407, carbomer, polysorbate 80, sodium benzoate, cetylpyridinium chloride, benzoic acid, titanium dioxide, blue 1, yellow 5

Questions?

1-800-492-7378

DISTR. BY PROCTER & GAMBLE,
CINCINNATI, OH 45202

PRINCIPAL DISPLAY PANEL - 155 g Tube Carton

Crest plus

ACTIVE FRESH

NET WT 5.5 OZ (155 g)

ANTICAVITY FLUORIDE TOOTHPASTE

+ WHITENING

scope®
KILLS UP TO 99.9%

OF BAD BREATH GERMS